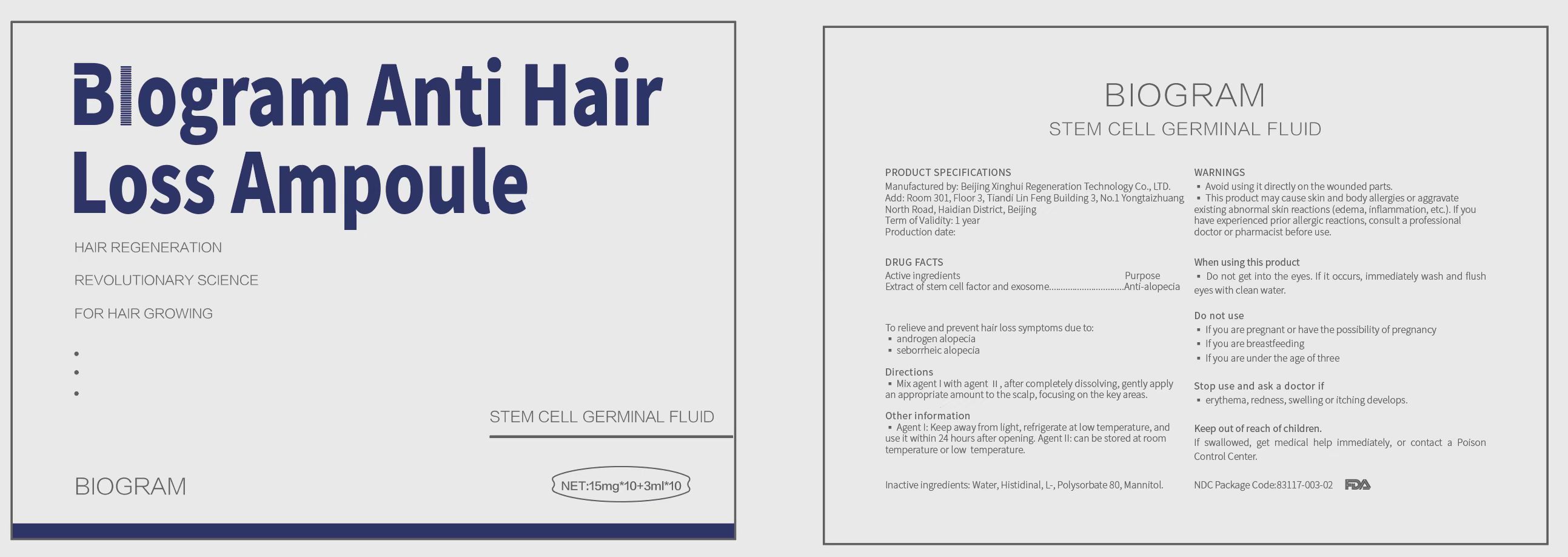 DRUG LABEL: Biogram Anti Hair Loss Ampoule
NDC: 83117-003 | Form: POWDER, FOR SOLUTION
Manufacturer: Beijing Xinghui Regeneration Technology Co., LTD.
Category: otc | Type: HUMAN OTC DRUG LABEL
Date: 20240624

ACTIVE INGREDIENTS: ALLOGENIC ADIPOSE DERIVED MESENCHYMAL STEM CELLS (MSCS) EXOSOMES 15 mg/3 mL
INACTIVE INGREDIENTS: WATER 2.85 mL/3 mL; HISTIDINAL, L- 0.009 mL/3 mL; POLYSORBATE 80 0.006 mL/3 mL; MANNITOL 0.135 mL/3 mL

Stem Cell Germinal Fluid

ACTIVE INGREDIENT

EXTRACT OF STEM CELL FACTOR AND EXOSOME.

WARNINGS

1. During the application of this product, if abnormal symptoms or side effects occur, such as erythema, redness, swelling or itching due to direct light, please seek for medical advice and consult a professional doctor immediately.
2. Avoid using it directly on the wounded parts.
3. Keep the product out of reach of children.
4. If it accidentally gets into the eyes, immediately wash and flush eyes with clean water.
5. This product may cause skin and body allergies or aggravate existing abnormal skin reactions (edema, inflammation, etc.). If you have experienced prior allergic reactions,consult a professional doctor or pharmacist before use.

Keep out of reach of children. If swallowed, get medical help immediately, or contact a Poison Control Center.

PURPOSE

To relieve and prevent hair loss symptoms due to:
• androgen alopecia
• seborrheic alopecia

Stop use and ask a doctor if condition worsens or does not improve after regular use as directed.

DOSAGE AND ADMINISTRATION

Mix agent I with agent Ⅱ, after completely dissolving, gently apply an appropriate amount to the scalp, focusing on the key areas.

Once daily.

DO NOT USE

• If you are pregnant or have the possibility of pregnancy
• If you are breastfeeding
• If you are under the age of three

STORAGE AND HANDLING

Agent I: Keep away from light, refrigerate at low temperature, and use it within 24 hours after opening. Agent II: can be stored at room temperature or low temperature.

INDICATIONS AND USAGE

To relieve and prevent hair loss symptoms due to androgen alopecia and seborrheic alopecia.

Mix agent I with agent Ⅱ, after completely dissolving, gently apply an appropriate amount to the scalp, focusing on the key areas.

INACTIVE INGREDIENT

WATER, MANNITOL, L-HISTIDINE, TWEEN-80

PACKAGE LABEL

20bottle in 1 box